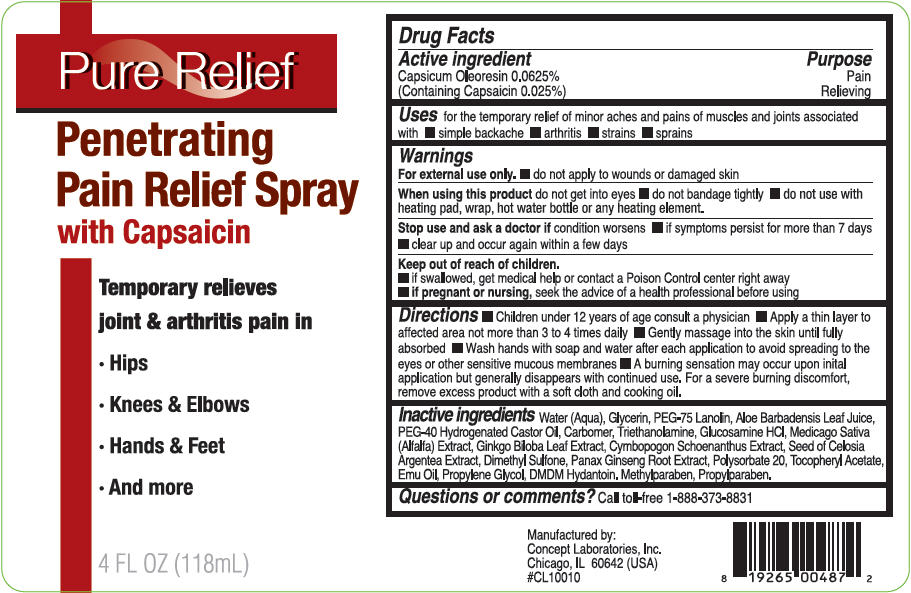 DRUG LABEL: Pure Relief 
NDC: 64058-118 | Form: GEL
Manufacturer: Concept Laboratories, Inc.
Category: otc | Type: HUMAN OTC DRUG LABEL
Date: 20140211

ACTIVE INGREDIENTS: Capsaicin 0.0295 g/118 mL
INACTIVE INGREDIENTS: Water; Glycerin; PEG-75 LANOLIN; DIMETHYL SULFONE; ALOE VERA LEAF; ALFALFA LEAF; CYMBOPOGON SCHOENANTHUS LEAF; GLUCOSAMINE HYDROCHLORIDE; GINKGO; POLYSORBATE 20; EMU OIL; DMDM HYDANTOIN; PROPYLENE GLYCOL; METHYLPARABEN; PROPYLPARABEN; TROLAMINE; .ALPHA.-TOCOPHEROL ACETATE; ASIAN GINSENG

Pure Relief
Penetrating Pain Relief Spray

Drug Facts

ACTIVE INGREDIENT

Active ingredient | Purpose
Capsicum Oleoresin 0.0625% | Pain
(Containing Capsaicin 0.025%) | Relieving

Uses

for the temporary relief of minor aches and pains of muscles and joints associated with

- simple backache
- arthritis
- strains
- sprains

Warnings

For external use only.

- do not apply to wounds or damaged skin

When using this product do not get into eyes

- do not bandage tightly
- do not use with heating pad, wrap, hot water bottle or any heating element.

Stop use and ask a doctor if condition worsens

- if symptoms persist for more than 7 days
- clear up and occur again within a few days

Keep out of reach of children.

- if swallowed, get medical help or contact a Poison Control center right away
- if pregnant or nursing, seek the advice of a health professional before using

Directions

- Children under 12 years of age consult a physician
- Apply a thin layer to affected area not more than 3 to 4 times daily
- Gently massage into the skin until fully absorbed
- Wash hands with soap and water after each application to avoid spreading to the eyes or other sensitive mucous membranes
- A burning sensation may occur upon inital application but generally disappears with continued use. For a severe burning discomfort, remove excess product with a soft cloth and cooking oil.

Inactive ingredients

Water (Aqua), Glycerin, PEG-75 Lanolin, Aloe Barbadensis Leaf Juice, PEG-40 Hydrogenated Castor Oil, Carbomer, Triethanolamine, Glucosamine HCl, Medicago Sativa (Alfalfa) Extract, Ginkgo Biloba Leaf Extract, Cymbopogon Schoenanthus Extract, Seed of Celosia Argentea Extract, Dimethyl Sulfone, Panax Ginseng Root Extract, Polysorbate 20, Tocopheryl Acetate, Emu Oil, Propylene Glycol, DMDM Hydantoin. Methylparaben, Propylparaben.

Questions or comments?

Call toll-free 1-888-373-8831

Manufactured by:
Concept Laboratories, Inc.
Chicago, IL 60642 (USA)
#CL10010

PRINCIPAL DISPLAY PANEL - 118 mL Bottle Label

Pure Relief

Penetrating
Pain Relief Spray
with Capsaicin

Temporary relieves
joint & arthritis pain in

- Hips
- Knees & Elbows
- Hands & Feet
- And more

4 FL OZ (118mL)